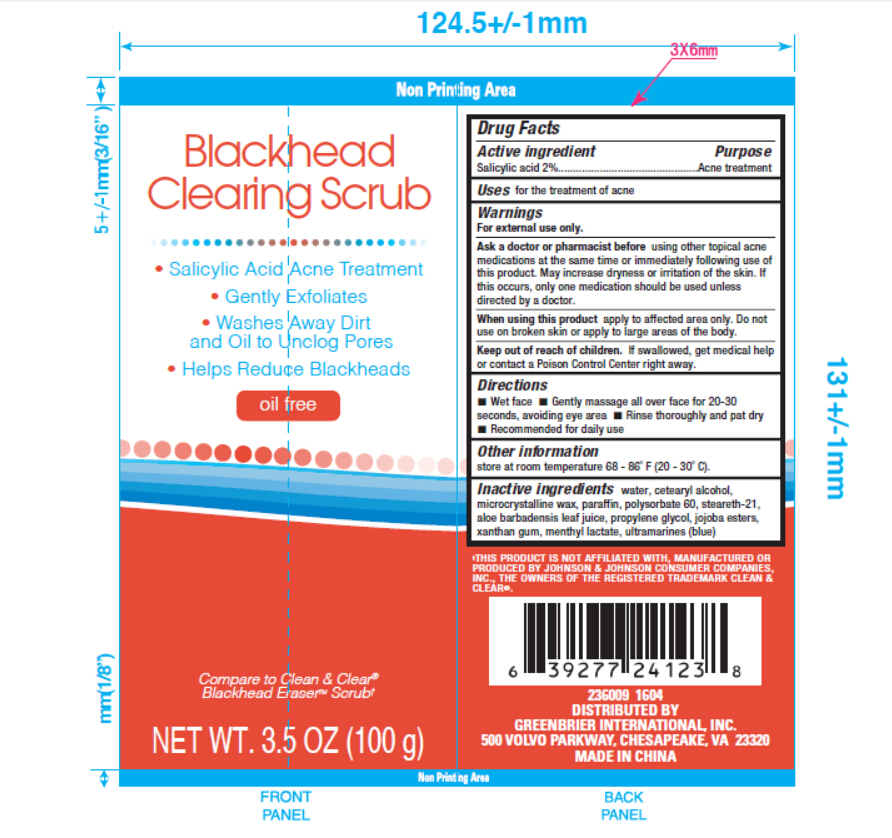 DRUG LABEL: Blackhead Cleaning Scrub
NDC: 58194-031 | Form: CREAM
Manufacturer: Shanghai Weierya Daily Chemicals Factory
Category: otc | Type: HUMAN OTC DRUG LABEL
Date: 20160113

ACTIVE INGREDIENTS: SALICYLIC ACID 2 g/100 g
INACTIVE INGREDIENTS: WATER; CETOSTEARYL ALCOHOL; MICROCRYSTALLINE WAX; PARAFFIN; POLYSORBATE 60; STEARETH-21; ALOE VERA LEAF; PROPYLENE GLYCOL; JOJOBA OIL, RANDOMIZED; XANTHAN GUM; MENTHYL LACTATE, (-)-

Drug Facts

Active ingredient

Salicylic acid 2%

Purpose

Acne treatment

INDICATIONS AND USAGE

Uses for the treatment of acne

Warnings

For external use only.

Flammable. Keep away from fire or flame.

Ask a doctor or pharmacist before using other topical

acne medications at the same time or immediately

following use of this product. May increase dryness or

irritation of the skin. If this occurs, only one medication

should be used unless directed by a doctor.

When using this product apply to affected area only.

Do not use on broken skin or apply to large areas of the

body.

Keep out of reach of children. If swallowed, get

medical help or contact a Poison Control Center right

away.

Directions

-Wet face -Gently massage all over face 20-30

seconds, avoiding eye area -Rinse thoroughly and pat dry

-Recommended for daily use

Other information store at room

temperature 68 - 86 F (20 - 30 C)

Inactive ingredients water, cetearyl alcohol,

microcrystalline wax, paraffin, polysorbate 60, steareth-21,

aloe barbadensis leaf juice, propylene glycol, jojoba esters,

xanthan gum, menthyl lactate, ultramarines (blue)